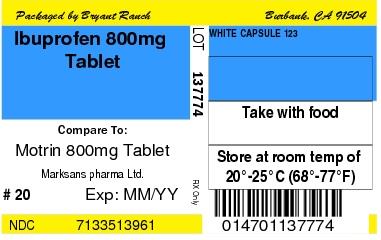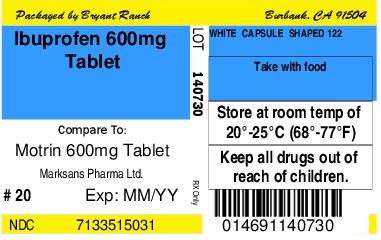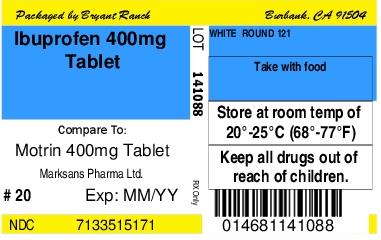 DRUG LABEL: IBUPROFEN
NDC: 71335-1396 | Form: TABLET, FILM COATED
Manufacturer: Bryant Ranch Prepack
Category: prescription | Type: HUMAN PRESCRIPTION DRUG LABEL
Date: 20200527

ACTIVE INGREDIENTS: IBUPROFEN 800 mg/1 1
INACTIVE INGREDIENTS: SILICON DIOXIDE; CROSCARMELLOSE SODIUM; MAGNESIUM STEARATE; MICROCRYSTALLINE CELLULOSE; POLYETHYLENE GLYCOL, UNSPECIFIED; POLYVINYL ALCOHOL, UNSPECIFIED; STARCH, CORN; TALC; TITANIUM DIOXIDE

IBUPROFEN 400 MG - 600 MG AND 800 MG TABLETS

HOW SUPPLIED

Product: 71335-1396

NDC: 71335-1396-0 84 TABLET, FILM COATED in a BOTTLE

NDC: 71335-1396-1 20 TABLET, FILM COATED in a BOTTLE

NDC: 71335-1396-2 15 TABLET, FILM COATED in a BOTTLE

NDC: 71335-1396-3 40 TABLET, FILM COATED in a BOTTLE

NDC: 71335-1396-4 21 TABLET, FILM COATED in a BOTTLE

NDC: 71335-1396-5 30 TABLET, FILM COATED in a BOTTLE

NDC: 71335-1396-6 90 TABLET, FILM COATED in a BOTTLE

NDC: 71335-1396-7 100 TABLET, FILM COATED in a BOTTLE

NDC: 71335-1396-8 120 TABLET, FILM COATED in a BOTTLE

NDC: 71335-1396-9 60 TABLET, FILM COATED in a BOTTLE

Product: 71335-1503

NDC: 71335-1503-0 21 TABLET, FILM COATED in a BOTTLE

NDC: 71335-1503-1 20 TABLET, FILM COATED in a BOTTLE

NDC: 71335-1503-2 15 TABLET, FILM COATED in a BOTTLE

NDC: 71335-1503-3 30 TABLET, FILM COATED in a BOTTLE

NDC: 71335-1503-4 40 TABLET, FILM COATED in a BOTTLE

NDC: 71335-1503-5 60 TABLET, FILM COATED in a BOTTLE

NDC: 71335-1503-6 90 TABLET, FILM COATED in a BOTTLE

NDC: 71335-1503-7 120 TABLET, FILM COATED in a BOTTLE

NDC: 71335-1503-8 50 TABLET, FILM COATED in a BOTTLE

NDC: 71335-1503-9 100 TABLET, FILM COATED in a BOTTLE

Product: 71335-1517

NDC: 71335-1517-1 20 TABLET, FILM COATED in a BOTTLE

NDC: 71335-1517-2 30 TABLET, FILM COATED in a BOTTLE

NDC: 71335-1517-3 40 TABLET, FILM COATED in a BOTTLE

NDC: 71335-1517-4 60 TABLET, FILM COATED in a BOTTLE

NDC: 71335-1517-5 90 TABLET, FILM COATED in a BOTTLE

NDC: 71335-1517-6 120 TABLET, FILM COATED in a BOTTLE

NDC: 71335-1517-7 100 TABLET, FILM COATED in a BOTTLE

NDC: 71335-1517-8 21 TABLET, FILM COATED in a BOTTLE

NDC: 71335-1517-9 15 TABLET, FILM COATED in a BOTTLE